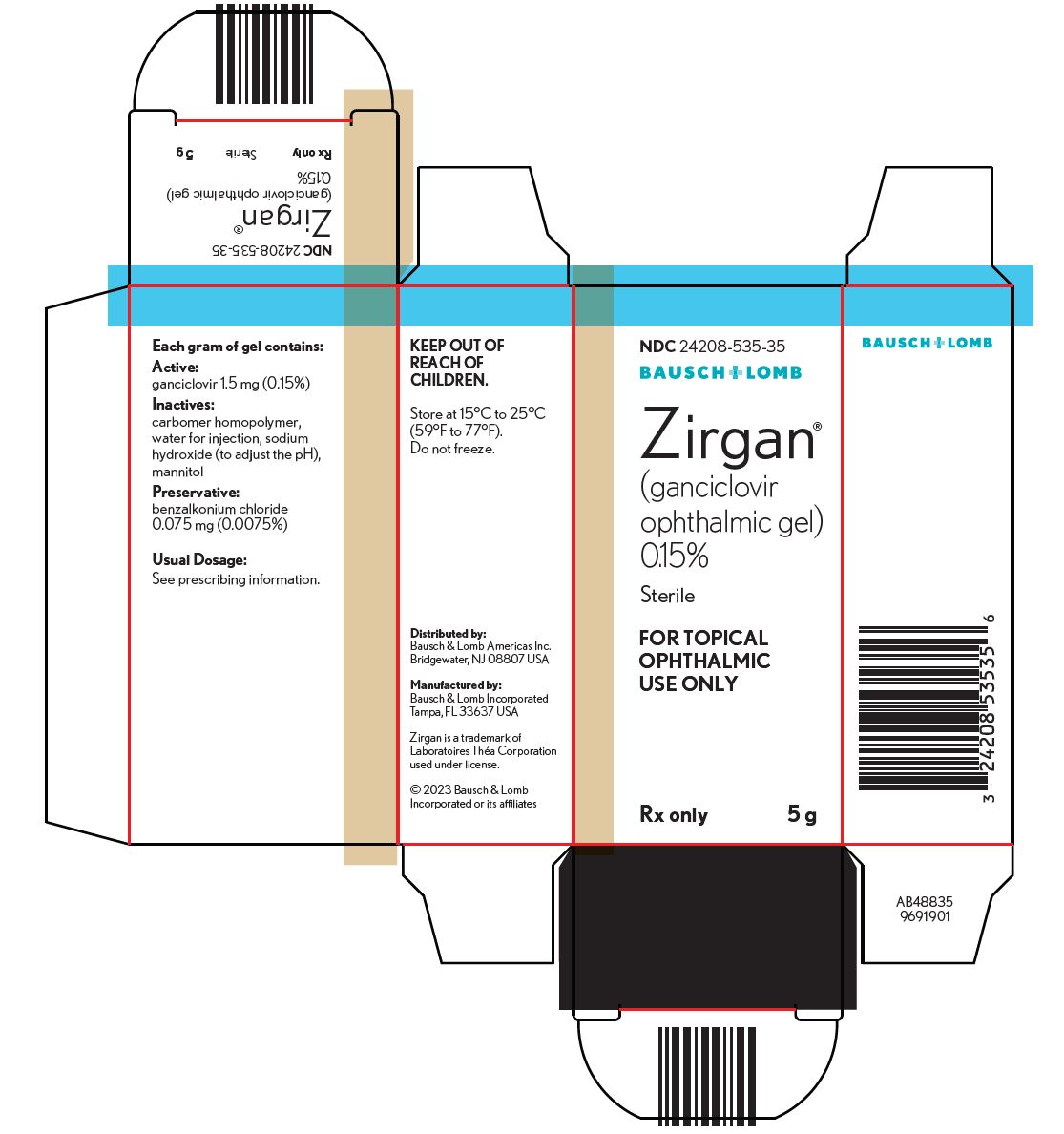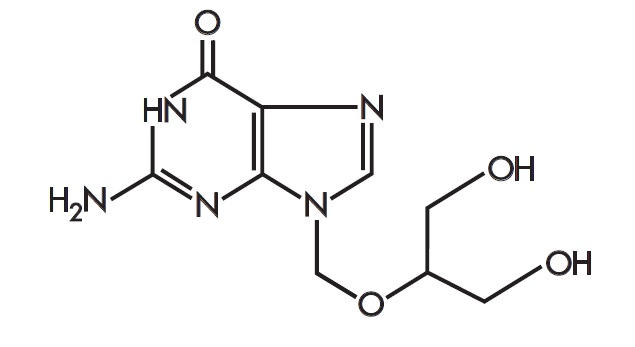 DRUG LABEL: ZIRGAN
NDC: 24208-535 | Form: GEL
Manufacturer: Bausch & Lomb Incorporated
Category: prescription | Type: HUMAN PRESCRIPTION DRUG LABEL
Date: 20260205

ACTIVE INGREDIENTS: GANCICLOVIR 1.5 mg/1 g
INACTIVE INGREDIENTS: CARBOMER HOMOPOLYMER TYPE B (ALLYL PENTAERYTHRITOL CROSSLINKED); BENZALKONIUM CHLORIDE; MANNITOL; WATER; SODIUM HYDROXIDE

HIGHLIGHTS OF PRESCRIBING INFORMATION

These highlights do not include all the information needed to use ZIRGAN® safely and effectively. See full prescribing information for ZIRGAN.
ZIRGAN (ganciclovir ophthalmic gel) 0.15%,
for topical ophthalmic use
Initial U.S. approval: 1989

1 INDICATIONS AND USAGE

ZIRGAN is a nucleoside analog antiviral indicated for the treatment of acute herpetic keratitis (dendritic ulcers) in adults and pediatric patients aged 2 years and older. (1)

2 DOSAGE AND ADMINISTRATION

Apply 1 drop in the affected eye 5 times per day (approximately every 3 hours while awake) until the corneal ulcer heals, and then 1 drop 3 times per day for 7 days. (2)

3 DOSAGE FORMS AND STRENGTHS

Ophthalmic gel: 0.15% ganciclovir. (3)

4 CONTRAINDICATIONS

None.

5 WARNINGS AND PRECAUTIONS

- ZIRGAN is indicated for topical ophthalmic use only. (5.1)
- Patients should not wear contact lenses if they have signs or symptoms of herpetic keratitis or during the course of therapy with ZIRGAN. (5.2)

6 ADVERSE REACTIONS

Most common adverse reactions were blurred vision (60%), eye irritation (20%), punctate keratitis (5%), and conjunctival hyperemia (5%). (6)

To report SUSPECTED ADVERSE REACTIONS, contact Bausch & Lomb Incorporated, at 1-800-553-5340 or FDA at 1-800-FDA-1088 or www.fda.gov/medwatch.

FULL PRESCRIBING INFORMATION

1 INDICATIONS AND USAGE

ZIRGAN is indicated for the treatment of acute herpetic keratitis (dendritic ulcers) in adults and pediatric patients aged 2 years and older.

2 DOSAGE AND ADMINISTRATION

The recommended dosage is 1 drop in the affected eye 5 times per day (approximately every 3 hours while awake) until the corneal ulcer heals, and then 1 drop 3 times per day for 7 days.

3 DOSAGE FORMS AND STRENGTHS

Ophthalmic gel: 0.15% ganciclovir.

4 CONTRAINDICATIONS

None.

5 WARNINGS AND PRECAUTIONS

5.1 Topical Ophthalmic Use Only

ZIRGAN is indicated for topical ophthalmic use only.

5.2 Avoidance of Contact Lenses

Patients should not wear contact lenses if they have signs or symptoms of herpetic keratitis or during the course of therapy with ZIRGAN.

5.3 Risk of Contamination

Do not allow the tip of the container to touch any surface, as this may contaminate the ointment. If pain develops, or if redness, itching, or inflammation becomes aggravated, the patient should be advised to consult a physician.

6 ADVERSE REACTIONS

Most common adverse reactions reported in patients were blurred vision (60%), eye irritation (20%), punctate keratitis (5%), and conjunctival hyperemia (5%).

8 USE IN SPECIFIC POPULATIONS

8.1 Pregnancy

Risk Summary

There are no available human data on use of ZIRGAN or ganciclovir during pregnancy to inform any drug-associated risk. Intravenous administration of ganciclovir to pregnant mice or rabbits during organogenesis or during the pre/postnatal period did not produce adverse embryofetal or offspring effects at clinically relevant doses (see Data) .

The background risk in the U.S. general population of major birth defects is 2 to 4% and the risk of miscarriage is 15 to 20% of clinically recognized pregnancies.

Data

Animal Data

Daily intravenous doses of ganciclovir were administered to pregnant mice [up to 108 mg/kg/day, approximately 1400 times the maximum recommended human ocular dose (RHOD) of 0.375 mg] and rabbits [up to 60 mg/kg/day, approximately 2400 times the maximum RHOD], and also to female mice [up to 90 mg/kg, approximately 1174 times the maximum RHOD] prior to mating, during gestation, and during lactation. Fetal resorptions were present in at least 85% of rabbits and mice. Additional effects observed in rabbits included fetal growth retardation, embryolethality, teratogenicity, and/or maternal toxicity. Teratogenic changes included cleft palate, anophthalmia/microphthalmia, aplastic organs (kidney and pancreas), hydrocephaly and brachygnathia. A maternal no observed adverse effect level (NOAEL) was observed at 36 mg/kg/day (approximately 470 times higher than the maximum RHOD, based on body surface area) in mice and at 6 mg/kg/day (approximately 240 times higher than the maximum RHOD, based on body surface area) in rabbits.

In pre/postnatal development studies in mice, there were maternal/fetal toxicity and embryolethality which included fetal effects of hypoplasia of the testes and seminal vesicles in the male offspring, as well as pathologic changes in the nonglandular region of the stomach. A maternal no observed adverse effect level (NOAEL) was observed at 20 mg/kg/day (approximately 261 times higher than the maximum RHOD, based on body surface area).

8.2 Lactation

Risk Summary

No data are available regarding the presence of ganciclovir in human milk, the effects on the breastfed infant, or the effects on milk production. It is not known whether topical ophthalmic ganciclovir administration could result in sufficient systemic absorption to produce detectable quantities in breast milk. Animal data indicate that ganciclovir is excreted in the milk of lactating rats. Caution should be exercised when ZIRGAN is administered to nursing mothers.

8.3 Females and Males of Reproductive Potential

Infertility

It is not known whether topical ophthalmic ganciclovir administration could result in sufficient absorption to impair fertility in humans. Animal data indicate decreased fertility in female mice following intravenous doses at 90 mg/kg/day, approximately 1174 times the maximum RHOD (based on body surface area), and decreased fertility and hypospermatogenesis in male mice and dogs following intravenous doses at 10 mg/kg/day for mice, approximately 130 times the maximum RHOD (based on body surface area), and 3.6 mg/kg/day for dogs, approximately 240 times the maximum RHOD (based on body surface area).

8.4 Pediatric Use

The safety and effectiveness of ZIRGAN for the treatment of acute herpetic keratitis (dendritic ulcers) have been established in pediatric patients aged 2 years and older. Use of ZIRGAN for this indication is supported by evidence from adequate and well-controlled studies.

The safety and effectiveness of ZIRGAN have not been established in pediatric patients below the age of 2 years.

8.5 Geriatric Use

No overall differences in safety or effectiveness have been observed between elderly and younger patients.

11 DESCRIPTION

ZIRGAN (ganciclovir ophthalmic gel) 0.15% contains ganciclovir, a nucleoside analog antiviral. ZIRGAN is a sterile, preserved, clear, colorless, ophthalmic gel for topical ophthalmic use.

The chemical name is 9-[[2-hydroxy-1-(hydroxymethyl)ethoxy]methyl]guanine (CAS number 82410-32-0). Ganciclovir is represented by the following structural formula:

Ganciclovir has a molecular weight of 255.23, and the empirical formula is C9H13N5O4.

Each gram of gel contains: ACTIVE: ganciclovir 1.5 mg (0.15%). INACTIVES: carbomer homopolymer, water for injection, sodium hydroxide (to adjust the pH to 7.2-7.6), mannitol. PRESERVATIVE: benzalkonium chloride 0.075 mg (0.0075%).

12 CLINICAL PHARMACOLOGY

12.1 Mechanism of Action

ZIRGAN is an antiviral drug [see Microbiology (12.4)].

12.3 Pharmacokinetics

The estimated maximum daily dose of ganciclovir administered as 1 drop, 5 times per day is 0.375 mg. Compared to maintenance doses of systemically administered ganciclovir of 900 mg (oral valganciclovir) and 5 mg/kg (IV ganciclovir), the ophthalmically administered daily dose is approximately 0.04% and 0.1% of the oral dose and IV doses, respectively, thus minimal systemic exposure is expected.

12.4 Microbiology

Mechanism of Action

ZIRGAN contains ganciclovir, a guanosine derivative that upon phosphorylation inhibits DNA replication by herpes simplex viruses (HSV). Ganciclovir is transformed by viral and cellular thymidine kinases (TK) to ganciclovir triphosphate, which works as an antiviral agent by inhibiting the synthesis of viral DNA in 2 ways: competitive inhibition of viral DNA-polymerase and direct incorporation into viral primer strand DNA, resulting in DNA chain termination and prevention of replication.

13 NONCLINICAL TOXICOLOGY

13.1 Carcinogenesis, Mutagenesis, Impairment of Fertility

Carcinogenesis

Ganciclovir was carcinogenic in the mouse at oral doses of 20 and 1,000 mg/kg/day (approximately 3,000 and 160,000 times the human ocular dose of 6.25 mcg/kg/day, assuming complete absorption). At the dose of 1,000 mg/kg/day there was a significant increase in the incidence of tumors of the preputial gland in males, forestomach (nonglandular mucosa) in males and females, and reproductive tissues (ovaries, uterus, mammary gland, clitoral gland, and vagina) and liver in females. At the dose of 20 mg/kg/day, a slightly increased incidence of tumors was noted in the preputial and harderian glands in males, forestomach in males and females, and liver in females. No carcinogenic effect was observed in mice administered ganciclovir at 1 mg/kg/day (160 times the human ocular dose). Except for histocytic sarcoma of the liver, ganciclovir-induced tumors were generally of epithelial or vascular origin. Although the preputial and clitoral glands, forestomach and harderian glands of mice do not have human counterparts, ganciclovir should be considered a potential carcinogen in humans.

Mutagenesis

Ganciclovir increased mutations in mouse lymphoma cells and DNA damage in human lymphocytes in vitroat concentrations between 50 to 500 and 250 to 2,000 mcg/mL, respectively.

In the mouse micronucleus assay, ganciclovir was clastogenic at doses of 150 and 500 mg/kg (IV) (24,000 to 80,000 times the human ocular dose) but not 50 mg/kg (8,000 times the human ocular dose). Ganciclovir was not mutagenic in the Ames Salmonella assay at concentrations of 500 to 5,000 mcg/mL.

Impairment of Fertility

Ganciclovir caused decreased mating behavior, decreased fertility, and an increased incidence of embryolethality in female mice following intravenous doses of 90 mg/kg/day (approximately 14,000 times the human ocular dose of 6.25 mcg/kg/day). Ganciclovir caused decreased fertility in male mice and hypospermatogenesis in mice and dogs following daily oral or intravenous administration of doses ranging from 0.2 to 10 mg/kg (30 to 1,600 times the human ocular dose).

14 CLINICAL STUDIES

In one open-label, randomized, controlled, multicenter clinical trial which enrolled 164 patients with herpetic keratitis, ZIRGAN was non-inferior to acyclovir ophthalmic ointment, 3% in patients with dendritic ulcers. Clinical resolution (healed ulcers) at Day 7 was achieved in 77% (55/71) for ZIRGAN versus 72% (48/67) for acyclovir, 3% (difference 5.8%, 95% CI - 9.6%-18.3%). In three randomized, single-masked, controlled, multicenter clinical trials which enrolled 213 total patients, ZIRGAN was non-inferior to acyclovir ophthalmic ointment, 3% in patients with dendritic ulcers. Clinical resolution at Day 7 was achieved in 72% (41/57) for ZIRGAN versus 69% (34/49) for acyclovir (difference 2.5%, 95% CI - 15.6%-20.9%).

16 HOW SUPPLIED/STORAGE AND HANDLING

ZIRGAN (ganciclovir ophthalmic gel) 0.15% is supplied as 5 grams of a sterile, preserved, clear, colorless, topical ophthalmic gel containing 0.15% of ganciclovir in a polycoated aluminum tube with a white polyethylene tip and cap and protective band (NDC 24208-535-35).

Storage

Store at 15°C to 25°C (59°F to 77°F). Do not freeze.

17 PATIENT COUNSELING INFORMATION

When to Consult a Physician

Advise patients to consult a physician if pain develops, or if redness, itching, or inflammation becomes aggravated.

Risk of Contamination

ZIRGAN is sterile when packaged. Advise patients to not allow the dropper tip to touch any surface, as this may contaminate the gel.

Avoidance of Contact Lenses

Advise patients to not wear contact lenses when using ZIRGAN.

Distributed by:

Bausch & Lomb Americas Inc.

Bridgewater, NJ 08807 USA

Manufactured by:

Bausch & Lomb Incorporated

Tampa, FL 33637 USA

Zirgan is a trademark of Laboratoires Théa Corporation used under license.

© 2025 Bausch & Lomb Incorporated or its affiliates

9224806

PACKAGE/LABEL PRINCIPAL DISPLAY PANEL

NDC24208-535-35

BAUSCH + LOMB

Zirgan

(ganciclovir

ophthalmic gel)

0.15%

Sterile

FOR TOPICAL

OPHTHALMIC

USE ONLY

Rx only

5 g

AB48835

9691901